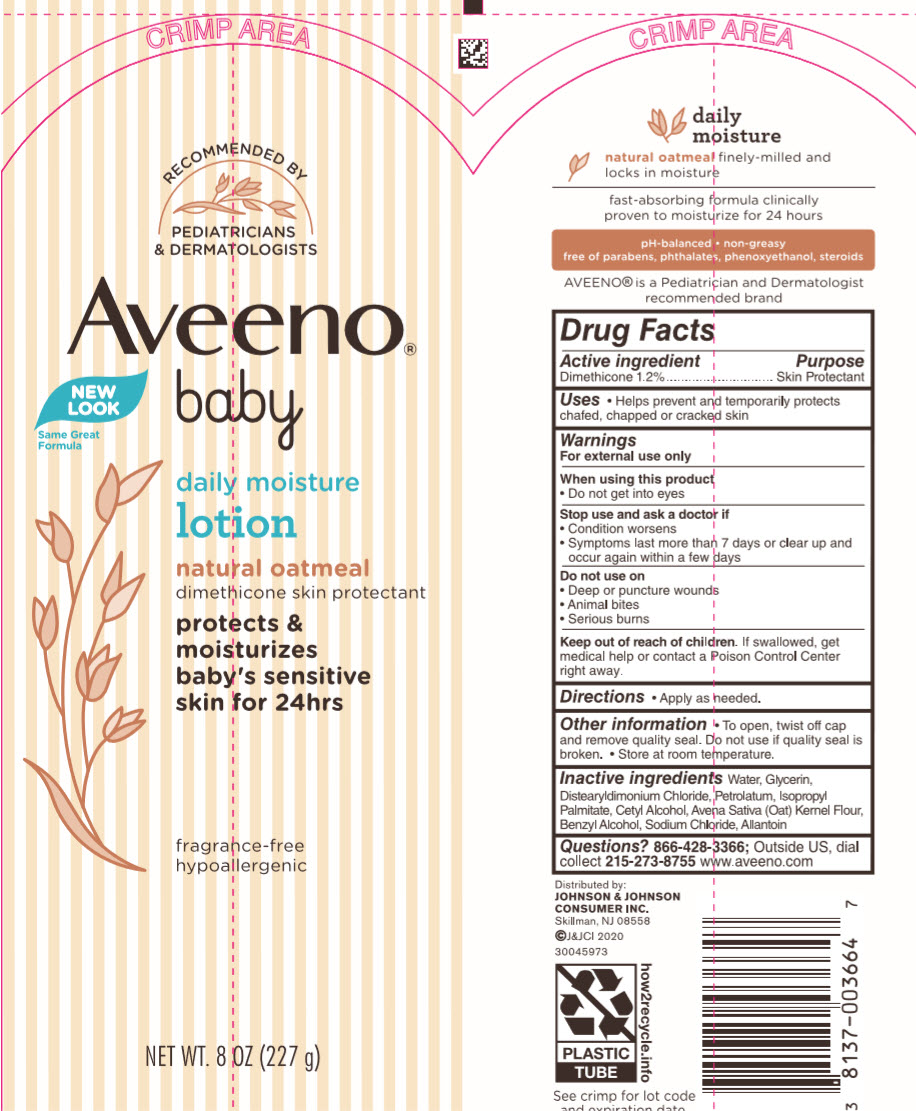 DRUG LABEL: Aveeno Baby Daily Moisture
NDC: 69968-0679 | Form: LOTION
Manufacturer: Kenvue Brands LLC
Category: otc | Type: HUMAN OTC DRUG LABEL
Date: 20241105

ACTIVE INGREDIENTS: DIMETHICONE 12 mg/1 g
INACTIVE INGREDIENTS: WATER; GLYCERIN; DISTEARYLDIMONIUM CHLORIDE; PETROLATUM; ISOPROPYL PALMITATE; CETYL ALCOHOL; OAT; BENZYL ALCOHOL; SODIUM CHLORIDE; ALLANTOIN

Aveeno® baby daily moisture lotion

Drug Facts

Active ingredient

Dimethicone 1.2%

Purpose

Skin Protectant

Uses

- Helps prevent and temporarily protects chafed, chapped or cracked skin

Warnings

For external use only

When using this product

- Do not get into eyes

Stop use and ask a doctor if

- Condition worsens
- Symptoms last more than 7 days or clear up and occur again within a few days

Do not use on

- Deep or puncture wounds
- Animal bites
- Serious burns

Keep out of reach of children. If swallowed, get medical help or contact a Poison Control Center right away.

Directions

- Apply as needed.

Other information

- To open, twist off cap and remove quality seal. Do not use if quality seal is broken.
- Store at room temperature.

Inactive ingredients

Water, Glycerin, Distearyldimonium Chloride, Petrolatum, Isopropyl Palmitate, Cetyl Alcohol, Avena Sativa (Oat) Kernel Flour, Benzyl Alcohol, Sodium Chloride, Allantoin

Questions?

866-428-3366; Outside US, dial collect 215-273-8755 www.aveeno.com

Distributed by:
JOHNSON & JOHNSON
CONSUMER INC.
Skillman, NJ 08558

PRINCIPAL DISPLAY PANEL - 227 g Tube Label

RECOMMENDED BY
PEDIATRICIANS
& DERMATOLOGISTS

Aveeno®
baby

NEW
LOOK
Same Great
Formula

daily moisture
lotion

natural oatmeal
dimethicone skin protectant

protects &
moisturizes
baby's sensitive
skin for 24hrs

fragrance-free
hypoallergic

NET WT. 8 OZ (227 g)